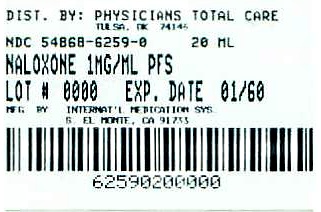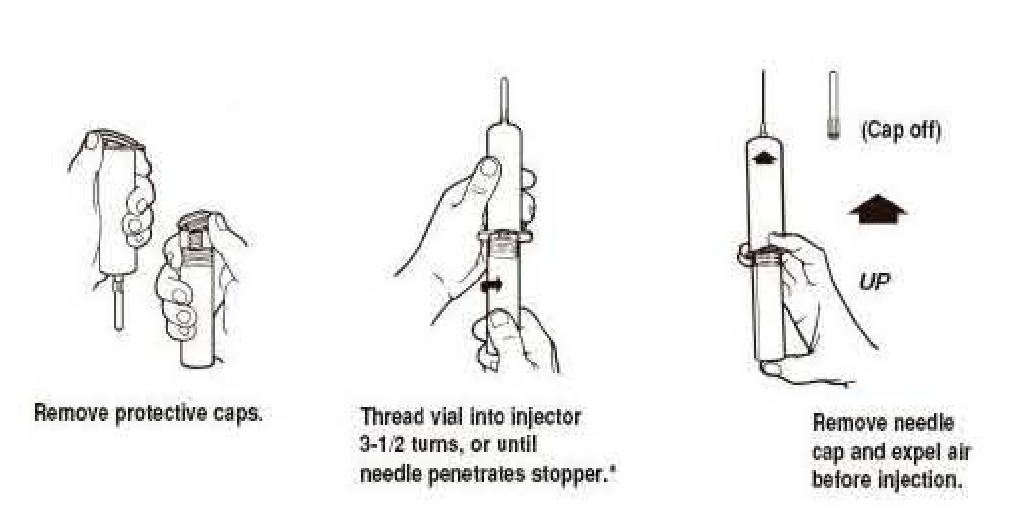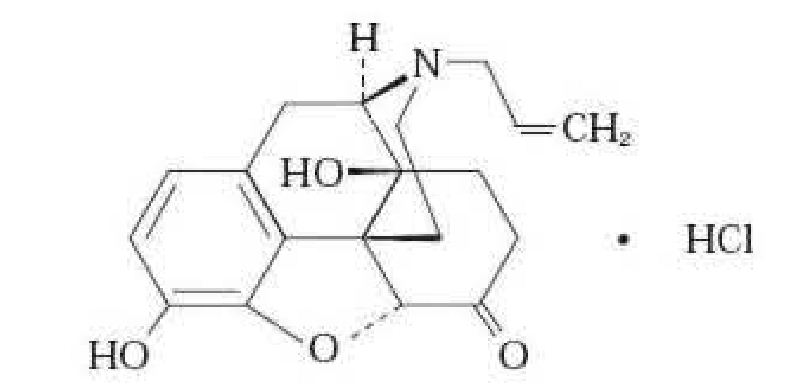 DRUG LABEL: Naloxone Hydrochloride
								
                        
NDC: 54868-6259 | Form: INJECTION
Manufacturer: Physicians Total Care, Inc.
Category: prescription | Type: HUMAN PRESCRIPTION DRUG LABEL
Date: 20110425

ACTIVE INGREDIENTS: Naloxone Hydrochloride 1 mg/1 mL
INACTIVE INGREDIENTS: Sodium Chloride 8.35 mg/1 mL; Hydrochloric Acid

Naloxone Hydrochloride 1mg/1ml 2ml Syringe

DESCRIPTION

Naloxone hydrochloride, a narcotic antagonist, is a synthetic congener of oxymorphone. In structure it differs from oxymorphone in that the methyl group on the nitrogen atom is replaced by an allyl group.
17-Allyl-4,5a-epoxy-3,14-dihydroxymorphinan-6-one hydrochloride
C19H21NO4• HCl 363.84

Naloxone hydrochloride occurs as a white to slightly off-white powder, and is soluble in water, in dilute acids, and in strong alkali; slightly soluble in alcohol; practically insoluble in ether and in chloroform.

Naloxone Hydrochloride Injection is available as a non-preserved sterile solution for intravenous, intramuscular or subcutaneous administration, in the 0.4 mg/mL and 1 mg/mL concentrations. Each mL of the 0.4 mg strength contains 8.6 mg of sodium chloride. Each mL of the 1 mg strength contains 8.35 mg of sodium chloride. The pH is adjusted with hydrochloric acid to meet USP limits of 3.0 to 4.5.

CLINICAL PHARMACOLOGY

Naloxone hydrochloride prevents or reverses the effects of opioids, including respiratory depression, sedation, and hypotension. Also, it can reverse the psychotomimetic and dysphoric effects of agonist-antagonist such as pentazocine.
Naloxone hydrochloride is an essentially pure narcotic antagonist, i.e., it does not possess the "agonistic" or morphine-like properties characteristic of other narcotic antagonists; naloxone does not produce respiratory depression, psychotomimetic effects or pupillary constriction. In the absence of narcotics or agonistic effects of other narcotic antagonists it exhibits essentially no pharmacologic activity.
Naloxone has not been shown to produce tolerance nor to cause physical or psychological dependence. In the presence of physical dependence on narcotics naloxone will produce withdrawal symptoms.

Mechanisms of Action
While the mechanism of action of naloxone is not fully understood, the preponderance of evidence suggests that naloxone antagonizes the opioid effects by competing for the same receptor sites.
When naloxone hydrochloride is administered intravenously the onset of action is generally apparent within two minutes; the onset of action is only slightly less rapid when it is administered subcutaneously or intramuscularly. The duration of action is dependent upon the dose and route of administration of naloxone hydrochloride. Intramuscular administration produces a more prolonged effect than intravenous administration. The requirement for repeat doses of naloxone, however, will also be dependent upon the amount, type and route of administration of the narcotic being antagonized.
Following parenteral administration naloxone hydrochloride is rapidly distributed in the body. It is metabolized in the liver, primarily by glucuronide conjugation, and excreted in urine. In one study the serum half-life in adults ranged from 30 to 81 minutes (mean 64 ± 12 minutes). In a neonatal study the mean plasma half-life was observed to be 3.1 ± 0.5 hours.

INDICATIONS & USAGE

Naloxone hydrochloride injection is indicated for the complete or partial reversal of narcotic depression, including respiratory depression, induced by opioids including natural and synthetic narcotics, propoxyphene, methadone and certain narcotic-antagonist analgesics: nalbuphine, pentazocine and butorphanol. Naloxone hydrochloride is also indicated for the diagnosis of suspected acute opioid overdosage.
Naloxone hydrochloride injection may be useful as an adjunctive agent to increase blood pressure in the management of septic shock.

CONTRAINDICATIONS

Naloxone hydrochloride injection is contraindicated in patients known to be hypersensitive to it.

WARNINGS

Naloxone hydrochloride should be administered cautiously to persons including newborns of mothers who are known or suspected to be physically dependent on opioids. In such cases an abrupt and complete reversal of narcotic effects may precipitate an acute abstinence syndrome.
The patient who has satisfactorily responded to naloxone should be kept under continued surveillance and repeated doses of naloxone should be administered, as necessary, since the duration of action of some narcotics may exceed that of naloxone.

Naloxone is not effective against respiratory depression due to non-opioid drugs. Reversal of buprenorphineinduced respiratory depression may be incomplete. If an incomplete response occurs, respirations should be mechanically assisted.

PRECAUTIONS

In addition to naloxone, other resuscitative measures such as maintenance of a free airway, artificial ventilation, cardiac massage, and vasopressor agents should be available and employed when necessary to counteract acute narcotic poisoning. Several instances of hypotension, hypertension, ventricular tachycardia and fibrillation, and pulmonary edema have been reported. These have occurred in postoperative patients, most of whom had pre-existing cardiovascular disorders or received other drugs which may have similar adverse cardiovascular effects. Although a direct cause-and-effect relationship has not been established, naloxone should be used with caution in patients with pre-existing cardiac disease or patients who have received potentially cardiotoxic drugs.

Carcinogenesis, Mutagenesis, Impairment of Fertility
Carcinogenicity and mutagenicity studies have not been performed with naloxone hydrochloride. Reproductive studies in mice and rats demonstrated no impairment of fertility.

Pregnancy
Teratogenic Effects
Pregnancy Category B
Reproduction studies performed in mice and rats at doses up to 1,000 times the human dose revealed no evidence of impaired fertility or harm to the fetus due to naloxone. There are, however, no adequate and well-controlled studies in pregnant women. Because animal reproduction studies are not always predictive of human response, naloxone hydrochloride should be used during pregnancy only if clearly needed.

Nursing Mothers
It is not known whether naloxone is excreted in human milk. Because many drugs are excreted in human milk, caution should be exercised when naloxone is administered to a nursing woman.

ADVERSE REACTIONS

Abrupt reversal of narcotic depression may result in nausea, vomiting, sweating, tachycardia, increased blood pressure, tremulousness, seizures and cardiac arrest. In postoperative patients, Iarger than necessary dosages of naloxone hydrochloride may result in significant reversal of analgesia, and in excitement. Hypotension, hypertension, ventricular tachycardia and fibrillation, and pulmonary edema have been associated with the use of naloxone postoperatively. (See "PRECAUTIONS" and "Usage in Adults, Postoperative Narcotic Depression.")

OVERDOSAGE

There is no clinical experience with naloxone hydrochloride overdosage in humans. In the mouse and rat the intravenous LD50 is 150 ± 5 mg/kg and 109 ± 4 mg/kg respectively. In acute subcutaneous toxicity studies in newborn rats the LD50 (95% CL) is 260 (228–296) mg/kg. Subcutaneous injection of 100 mg/kg/day in rats for 3 weeks produced only transient salivation and partial ptosis following injection: no toxic effects were seen at 10 mg/kg/day for 3 weeks.

DOSAGE AND ADMINISTRATION

Naloxone hydrochloride injection may be administered intravenously, intramuscularly, or subcutaneously. The most rapid onset of action is achieved by intravenous administration, and it is recommended in emergency situations. Since the duration of action of some narcotics may exceed that of naloxone, the patient should be kept under continued surveillance and repeated doses of naloxone should be administered, as necessary.

Intravenous Infusion
Naloxone hydrochloride injection may be diluted for intravenous infusion in Sodium Chloride Injection 0.9% or Dextrose Injection 5%. The addition of 2 mg of naloxone in 500 mL of either solution provides a concentration of 0.004 mg/mL. Mixtures should be used within 24 hours. After 24 hours, the remaining unused solution must be discarded. The rate of administration should be titrated in accordance with the patient's response. Parenteral drug products should be inspected visually for particulate matter and discoloration prior to administration whenever solution and container permit. Naloxone hydrochloride injection should not be mixed with preparations containing bisulfite, metabisulfite, long-chain or high-molecular-weight anions, or any solution having an alkaline pH. No drug or chemical agent should be added to naloxone hydrochloride injection unless its effect on the chemical and physical stability of the solution has first been established.

USAGE IN ADULTS
Narcotic Overdose—Known or Suspected
An initial dose of 0.4 mg to 2 mg of naloxone hydrochloride may be administered intravenously. If the desired degree of counteraction and improvement in respiratory functions is not obtained, it may be repeated at 2 to 3 minute intervals. If no response is observed after 10 mg of naloxone hydrochloride have been administered, the diagnosis of narcotic-induced or partial narcotic-induced toxicity should be questioned. Intramuscular or subcutaneous administration may be necessary if the intravenous route is not available.
Postoperative Narcotic Depression
For the partial reversal of narcotic depression following the use of narcotics during surgery, smaller doses of naloxone hydrochloride are usually sufficient. The dose of naloxone hydrochloride should be titrated according to the patients response. Naloxone hydrochloride should be injected in increments of 0.1 to 0.2 mg intravenously at two to three minute intervals to the desired degree of reversal—i.e., adequate ventilation and alertness without significant pain or discomfort. Larger than necessary dosage of naloxone may result in significant reversal of analgesia and increase in blood pressure. Similarly, too rapid reversal may induce nausea, vomiting, sweating, or circulatory stress.
Repeat doses of naloxone may be required within one- to two-hour intervals depending upon the amount, type (i.e., short- or longacting) and time interval since last administration of narcotic. Supplemental intramuscular doses have been shown to produce a longer lasting effect.
USAGE IN CHILDREN
Narcotic Overdose—Known or Suspected
The usual initial dose in children is 0.01 mg/kg body weight given I.V. If this dose does not result in the desired degree of clinical improvement, a subsequent dose of 0.1 mg/kg body weight may be administered. If an I.V. route of administration is not available, naloxone may be administered I.M. or S.C. in divided doses. If necessary, naloxone hydrochloride injection can be diluted with sterile water for injection.
Postoperative Narcotic Depression
Follow the recommendations and cautions under "Adult Postoperative Depression." For the initial reversal of respiratory depression naloxone hydrochloride should be injected in increments of 0.005 mg to 0.01 mg intravenously at two- to three-minute intervals to the desired degree of reversal.
USAGE IN NEONATES
When using naloxone hydrochloride injection in Neonates a product containing 0.02 mg/mL should be used.

Narcotic-Induced Depression
The usual initial dose is 0.01 mg/kg body weight administered I.V., I.M., or S.C. This dose may be repeated in accordance with adult administration guidelines for postoperative narcotic depression.

HOW SUPPLIED

Available as follows:
1 mg/mL
2 mL single dose disposable Luer-Jet™ Luer-Lock Prefilled Syringe.
Shrink Wrapped Packages of 20 NDC 54868-6259-0 (contains no preservative)

Syringe Assembly Directions
The MIN-I-JET® syringe with needle, illustrated below, is the basic unit upon which all the other syringe systems are built; slight adaptations and/ or additional auxiliary parts createthe other syringe systems. Assembly directions remain essentially the same.

USE ASEPTIC TECHNIQUE
Do not assemble until ready to use.

*CAUTION: IMPROPER ENGAGING MAY CAUSE GLASS BREAKAGE AND SUBSEQUENT INJURY.
Protect from light. Store at controlled room temperature 15° to 30°C (59° to 86°F) [see USP].

Rx Only

INTERNATIONAL MEDICATION SYSTEMS, LIMITED
SO. EL MONTE, CA 91733, U.S.A
An Amphastar Pharmaceuticals Company
6914660M
REV. 8-01

Relabeling of "Additional" label by:
Physicians Total Care, Inc.
Tulsa, OK 74146

PRINCIPAL DISPLAY PANEL

Naloxone Hydrochloride injection USP

1 mg/mL

(2 mL x 10 PFS)

NDC 54868-6256-0